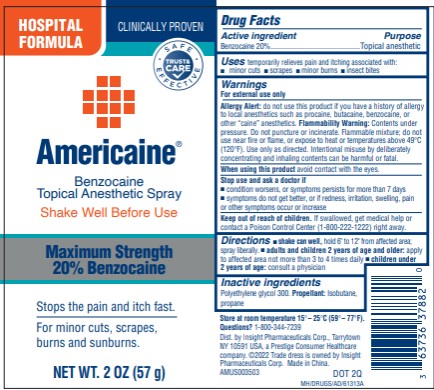 DRUG LABEL: Americaine
NDC: 63736-378 | Form: AEROSOL, SPRAY
Manufacturer: Insight Pharmaceuticals LLC
Category: otc | Type: HUMAN OTC DRUG LABEL
Date: 20251023

ACTIVE INGREDIENTS: BENZOCAINE 11.4 g/57 g
INACTIVE INGREDIENTS: ISOBUTANE; POLYETHYLENE GLYCOL 300; PROPANE

Americaine Topical Spray

Americaine®
Benzocaine
Topical Anesthetic Spray

Drug Facts

Active ingredient

Benzocaine 20%

Purpose

Topical Anesthetic

Uses

temporarily relieves pain and itching associated with:

- minor cuts
- scrapes
- minor burns
- insect bites

Warnings

For external use only
Allergy Alert

do not use

this product if you have a history of allergy to local anesthetics such as procaine, butacaine, benzocaine, or other “caine” anesthetics.

Flammability Warning

Contents under pressure. Do not puncture or incinerate. Flammable mixture; do not use near fire or flame, or expose to heat or temperatures above 49°C (120°F). Use only as directed. Intentional misuse by deliberately concentrating and inhaling contents can be harmful or fatal.

When using this product

avoid contact with the eyes

Stop use and ask a doctor if

- condition worsens, or symptoms persists for more than 7 days
- symptoms do not get better, or if redness, irritation, swelling, pain or other symptoms occur or increase

Keep out of reach of children.

If swallowed, get medical help or contact a Poison Control Center (1-800-222-1222) right away.

Directions

- shake can well, hold 6" to 12" from affected area; spray liberally.
- adults and children 2 years of age and older: apply to affected area not more than 3 to 4 times daily
- children under 2 years of age: consult a physician

Inactive ingredients

Polyethylene glycol 300
Propellant: Isobutane, , propane

Store at room temperature 15°– 25°C (59°– 77°F).

Questions?

1-800-344-7239

PRINCIPAL DISPLAY PANEL - 2 OZ Spray Label

Americaine®
Benzocaine
Topical Anesthetic Spray
NET WT. 2 OZ (57 G)